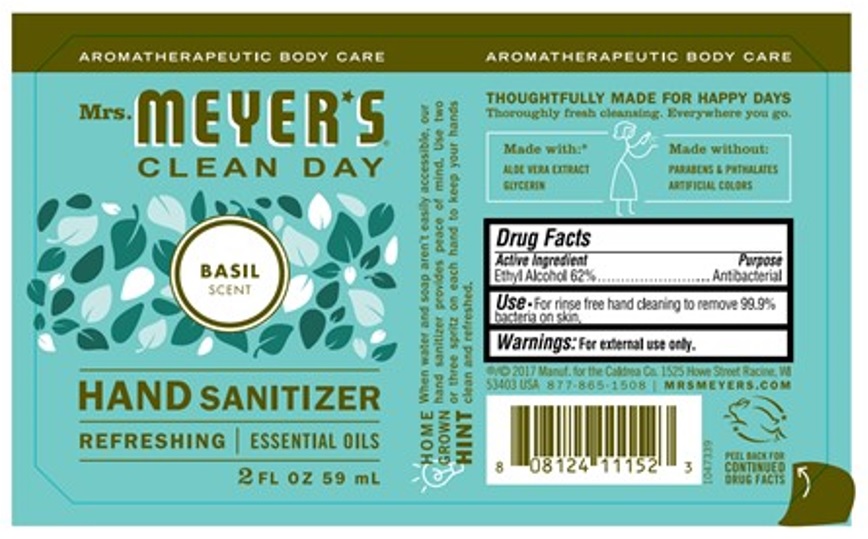 DRUG LABEL: Mrs. Meyers Hand Sanitizer Basil Scent
NDC: 68534-002 | Form: LIQUID
Manufacturer: METROPOLITANGRAPHIC ARTS, Inc.
Category: otc | Type: HUMAN OTC DRUG LABEL
Date: 20251021

ACTIVE INGREDIENTS: ALCOHOL 62 mL/100 mL
INACTIVE INGREDIENTS: GLYCERIN; WATER; ALOE VERA LEAF; BASIL OIL; PARSLEY SEED OIL; WHITE PEPPER OIL; ETHYLENE BRASSYLATE; LINALOOL, (+/-)-; .GAMMA.-UNDECALACTONE; GERANIOL; 4-METHYL-3-DECEN-5-OL, (3E)-; 3-HEXEN-1-OL, (3Z)-; METHYL DIHYDROJASMONATE (SYNTHETIC); TETRAMETHYL ACETYLOCTAHYDRONAPHTHALENES

Active ingredient

Ethyl Alcohol 62%

Purpose

Antibacterial

Uses

For rinse free hand cleaning to remove 99.9% bacteria on skin

Warning

For External use only. Eye and Skin Irritation, Flammable Liquid & Vapor

Direction

Skin and Eye Care, Handling & Storage

Inactive ingredients

Water, glycerin, Aloe barbadensis leaf juice, Ocimum Basilicum (Basil) oil, Carum petroselinum (parsley) seed oil, Piper Nigrum (Black papper) seed oil [ Fragrance: ethylene brassylate ', Linalool, gamma-undecalactone, geraniol, methyl decenol, 3-hexenol, methyldihydrojasmonate, tetramethyl acetyloctahydronaphthalenes]